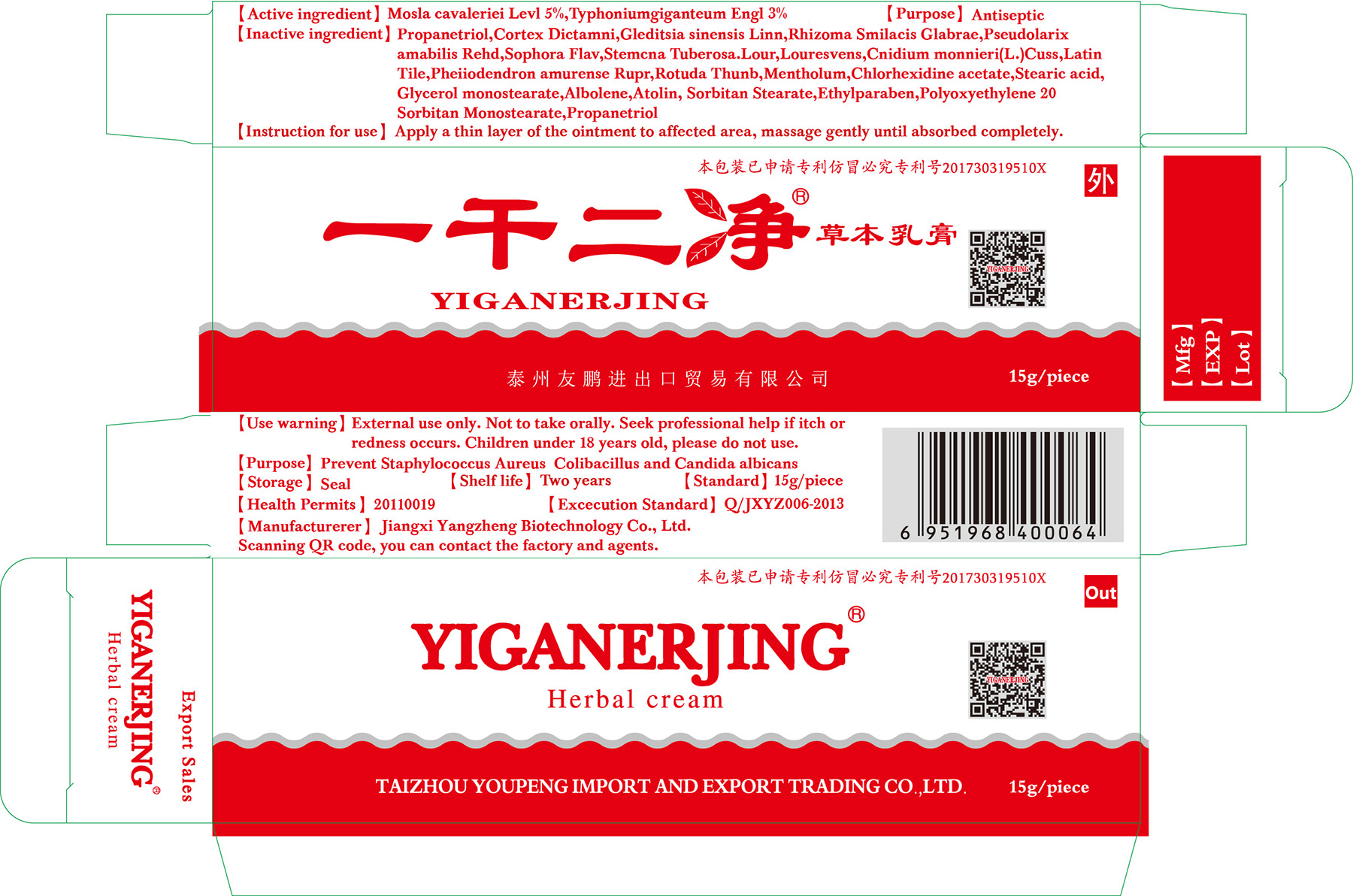 DRUG LABEL: Yiganerjing Herbal
NDC: 71939-001 | Form: CREAM
Manufacturer: TAIZHOU YOUPENG IMPORT AND EXPORT TRADING CO., LTD
Category: otc | Type: HUMAN OTC DRUG LABEL
Date: 20180209

ACTIVE INGREDIENTS: TYPHONIUM GIGANTEUM WHOLE 3 g/100 g
INACTIVE INGREDIENTS: GLEDITSIA SINENSIS FRUIT; PSEUDOLARIX AMABILIS WHOLE; SOPHORA FLAVESCENS WHOLE; CNIDIUM MONNIERI FRUIT; MENTHOL; CHLORHEXIDINE ACETATE; STEARIC ACID; ETHYLPARABEN

Purpose:

Prevent bacteria growth

Warning:

External use only. Not to take orally. Seek professional help if itch or redness occurs.

KEEP OUT OF REACH OF CHILDREN

Children under 18 years old, please do not use.

DOSAGE AND ADMINISTRATION

Instruction for use:

Apply a thin layer of the ointment to affected area, massage gently until absorbed completely.

Inactive Ingredients:

Propanetriol,Cortex Dictamni,Gleditsia sinensis Linn,Rhizoma Smilacis Glabrae,Pseudolarix amabilis Rehd,Sophora Flav,Stemcna Tuberosa.Lour,Louresvens,Cnidium monnieri(L.)Cuss,Latin Tile,Pheiiodendron amurense Rupr,Rotuda Thunb,Mentholum,Chlorhexidine acetate,Stearic acid, Glycerol monostearate,Albolene,Atolin, Sorbitan Stearate,Ethylparaben,Polyoxyethylene 20 Sorbitan Monostearate,Propanetriol